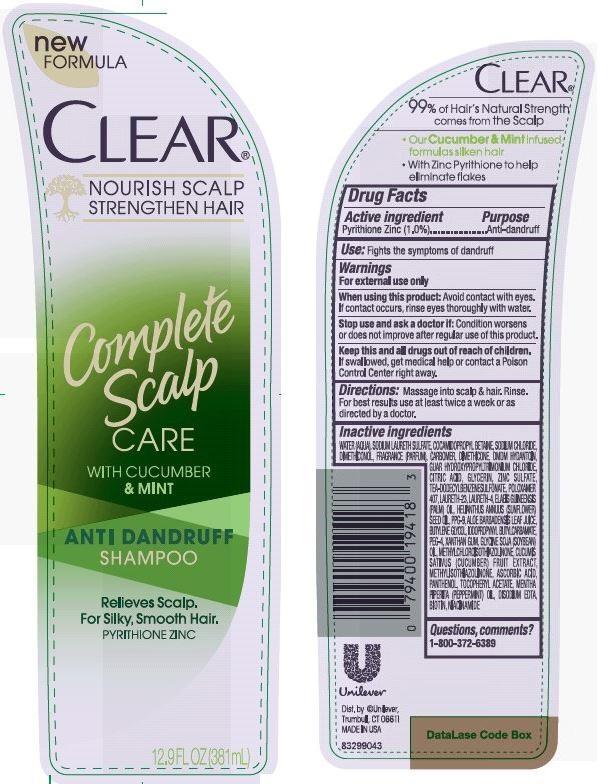 DRUG LABEL: Clear
NDC: 64942-1434 | Form: SHAMPOO
Manufacturer: Conopco Inc. d/b/a Unilever
Category: otc | Type: HUMAN OTC DRUG LABEL
Date: 20150917

ACTIVE INGREDIENTS: Pyrithione Zinc 1.0 g/100 mL
INACTIVE INGREDIENTS: WATER; SODIUM LAURETH SULFATE; COCAMIDOPROPYL BETAINE; SODIUM CHLORIDE; DMDM HYDANTOIN; TRIETHANOLAMINE DODECYLBENZENESULFONATE; SUNFLOWER OIL; CITRIC ACID MONOHYDRATE; PPG-9; METHYLCHLOROISOTHIAZOLINONE; METHYLISOTHIAZOLINONE; GUAR HYDROXYPROPYLTRIMONIUM CHLORIDE (1.7 SUBSTITUENTS PER SACCHARIDE); ZINC SULFATE; DIMETHICONOL (41 MPA.S); DIMETHICONE; POLOXAMER 407; LAURETH-23; LAURETH-4; .ALPHA.-TOCOPHEROL ACETATE, D-; PALM OIL; BUTYLENE GLYCOL; IODOPROPYNYL BUTYLCARBAMATE; XANTHAN GUM; SOYBEAN OIL; BIOTIN; NIACINAMIDE

Clear Complete Scalp Care Antidandruff Shampoo

Active Ingredient

Pyrithione Zinc (1.0%)

Purpose

Anti-dandruff

INDICATIONS AND USAGE

Use: Fights the symptoms of dandruff

Warnings
For external use only

When using this product: Avoid contact with eyes. If contact occurs, rinse eyes thoroughly with water.

Stop use and ask a doctor if: Condition worsens or does not improve after regular use of this product.

KEEP OUT OF REACH OF CHILDREN

Keep this and all drugs out of reach of children. If swallowed, get medical help or contact a Poison Control Center right away.

DOSAGE AND ADMINISTRATION

Directions: Massage into scalp & hair. Rinse. For best results use at least twice a week or as directed by a doctor.

Inactive Ingredients

Water (Aqua), Sodium Laureth Sulfate, Cocamidopropyl Betaine, Sodium Chloride, Dimethiconol, Fragrance (Parfum), Carbomer, Dimethicone, DMDM Hydantoin, Guar Hydroxypropyltrimonium Chloride, Citric Acid, Glycerin, Zinc Sulfate, TEA-Dodecylbenzenesulfonate, Poloxamer 407, Laureth-23, Laureth-4, Elaeis Guineensis (Palm) Oil, Helianthus Annuus (Sunflower) Seed Oil, PPG-9, Aloe Barbadensis Leaf Juice, Butylene Glycol, Iodopropynyl Butylcarbamate, PEG-4, Xanthan Gum, Glycine Soja (Soybean) Oil, Methylchloroisothiazolinone, Cucumis Sativus (Cucumber) Fruit Extract, Methylisothiazolinone, Ascorbic Acid, Panthenol, Tocopheryl Acetate, Mentha Piperita (Peppermint) Oil, Disodium EDTA, Biotin, Niacinamide

Questions, comments?1-800-372-6389